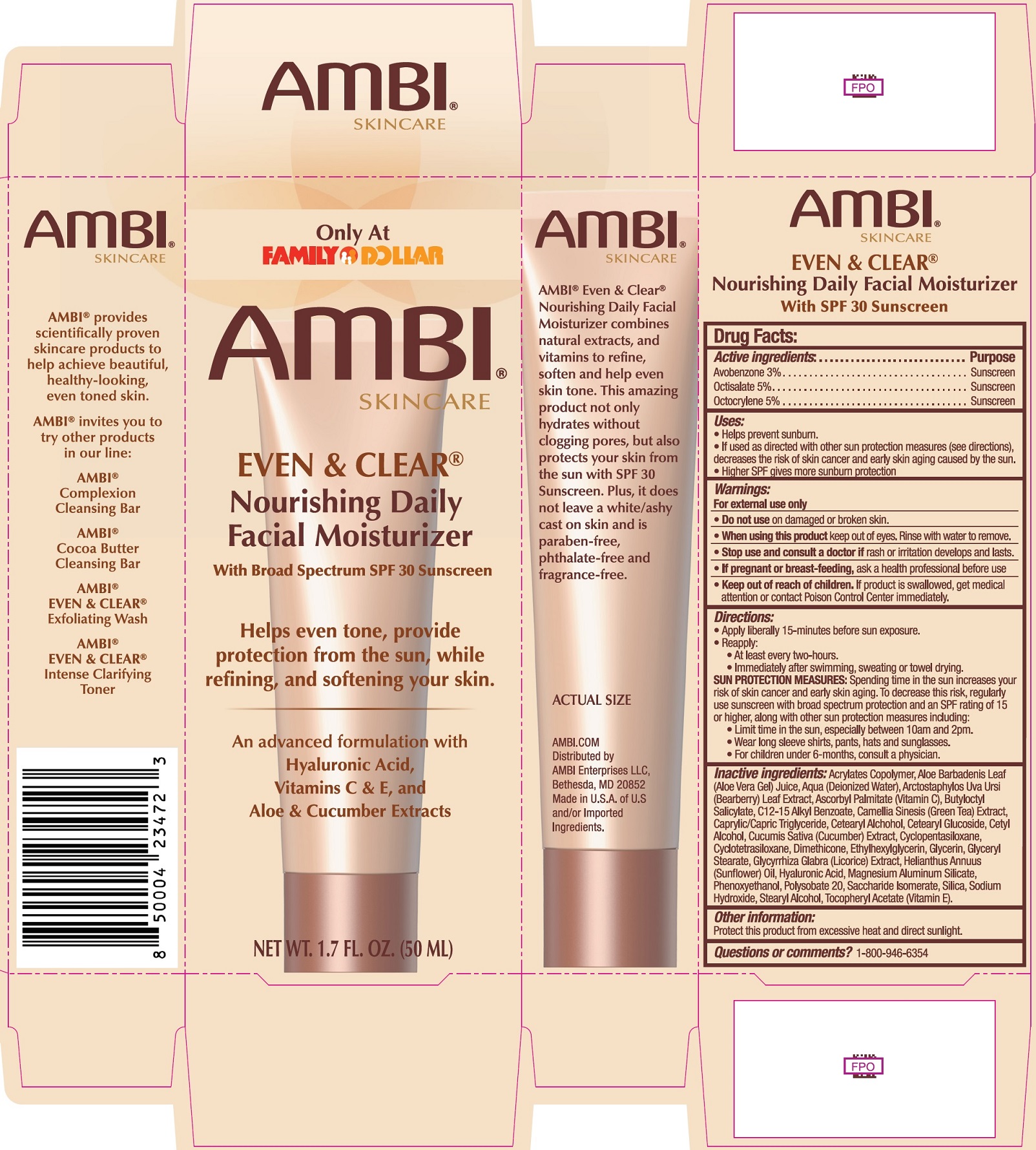 DRUG LABEL: AMBI Even and Clear Facial Moisturizer SPF-30
NDC: 73453-233 | Form: CREAM
Manufacturer: AMBI Enterprises LLC
Category: otc | Type: HUMAN OTC DRUG LABEL
Date: 20250724

ACTIVE INGREDIENTS: AVOBENZONE 30 mg/1 mL; OCTISALATE 50 mg/1 mL; OCTOCRYLENE 50 mg/1 mL
INACTIVE INGREDIENTS: ALOE VERA LEAF; WATER; ARCTOSTAPHYLOS UVA-URSI LEAF; ASCORBYL PALMITATE; BUTYLOCTYL SALICYLATE; ALKYL (C12-15) BENZOATE; GREEN TEA LEAF; MEDIUM-CHAIN TRIGLYCERIDES; CETOSTEARYL ALCOHOL; CETEARYL GLUCOSIDE; CETYL ALCOHOL; CUCUMBER; CYCLOMETHICONE 5; DIMETHICONE; ETHYLHEXYLGLYCERIN; GLYCERIN; GLYCERYL MONOSTEARATE; LICORICE; HELIANTHUS ANNUUS FLOWERING TOP; HYALURONIC ACID; MAGNESIUM ALUMINUM SILICATE; PHENOXYETHANOL; POLYSORBATE 20; SACCHARIDE ISOMERATE; SILICON DIOXIDE; SODIUM HYDROXIDE; STEARYL ALCOHOL; .ALPHA.-TOCOPHEROL ACETATE

AMBI Even & Clear Facial Moisturizer SPF-30

Active ingredients:

Avobenzone 3% Octisalate 5% Octocrylene 5%

Purpose

Sunscreen

Uses:

- Helps prevent sunburn.
- If used as directed with other sun protection measures (see directions), decreases the risk of skin cancer and early skin aging caused by the sun.
- Higher SPF gives more sunburn protection

Warnings:

For external use only

Do not use

- on damaged or broken skin.

When using this product

keep out of eyes. Rinse with water to remove.

Stop use and consult a doctor if

rash or irritation develops and lasts.

If pregnant or breast-feeding,

ask a health professional before use

Keep out of reach of children.

If product is swallowed, get medical attention or contact Poison Control Center immediately.

Directions:

- Apply liberally 15-minutes before sun exposure.
- Reapply:
- At least every two-hours.
- Immediately after swimming, sweating or towel drying.
- Spending time in the sun increases your risk of skin cancer and early skin aging. To decrease this risk, regularly use sunscreen with broad spectrum protection and an SPF rating of 15 or higher, along with other sun protection and other sun measures including: SUN PROTECTION MEASURES:
- Limit time in the sun, especially between 10 am and 2 pm.
- Wear long sleeve shirts, pants, hats and sunglasses.
- For children under 6-months, consult a physician.

Inactive ingredients:

Acrylates Copolymer, Aloe Barbadensis Leaf (Aloe Vera Gel) Juice, Aqua (Deionized Water), Arctostaphylos Uva Ursi (Bearberry) Leaf Extract, Ascorbyl Palmitate (Vitamin C), Butyloctyl Salicylate, C12-15 Alkyl Benzoate, Camellia Sinensis (Green Tea) Extract, Caprylic/Capric Triglyceride, Cetearyl Alcohol, Cetearyl Glucoside, Cetyl Alcohol, Cucumis Sativa (Cucumber) Extract, Cyclopentasiloxane, Cyclotetrasiloxane, Dimethicone, Ethylhexylglycerin, Glycerin, Glyceryl Stearate, Glycyrrhiza Glabra (Licorice) Extarct, Helianthus Annuus (Sunflower) Oil, Hyaluronic Acid, Magnesium Aluminum Silicate, Phenoxyethanol, Polysorbate 20, Saccharide Isomerate, Silica, Sodium Hydroxide, Stearyl Alcohol, Tocopheryl Acetate (Vitamin E).

Other information:

Protect this product from excessive heat and direct sunlight.

Questions or comments?

1-800-946-6354